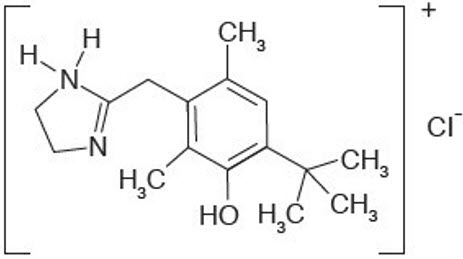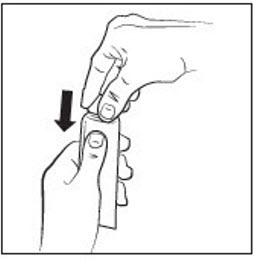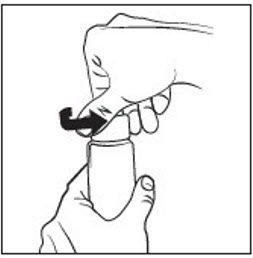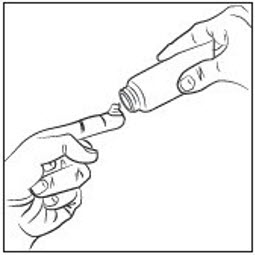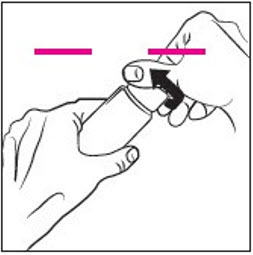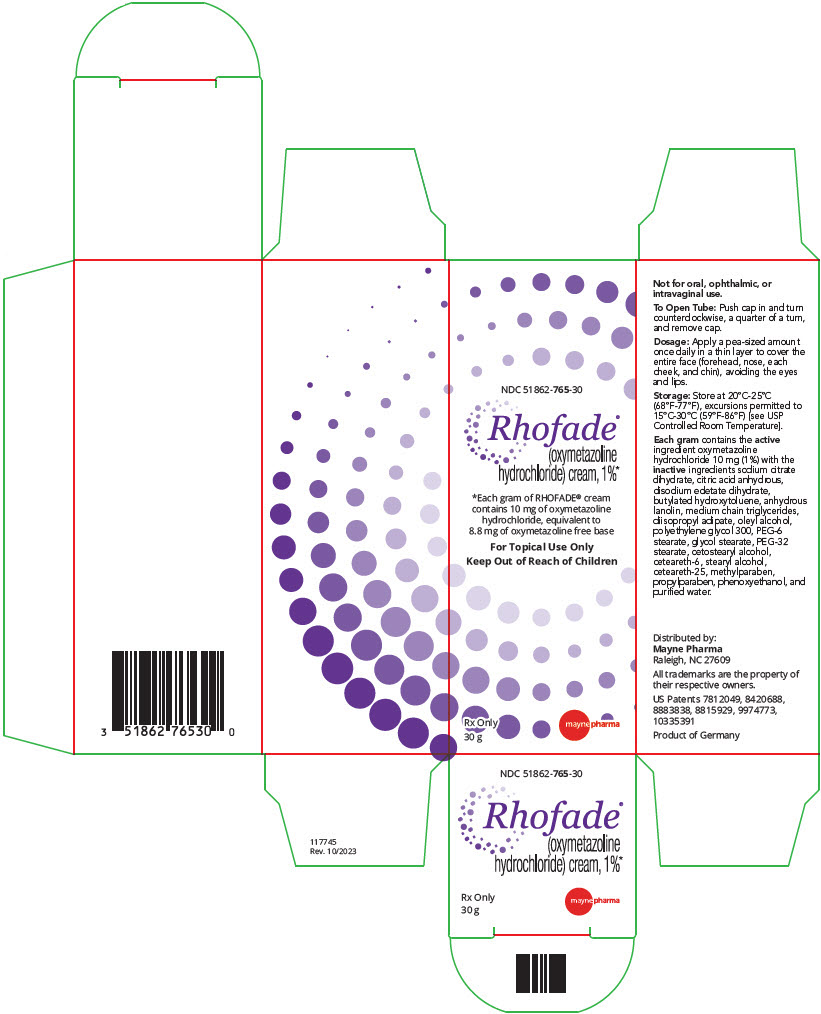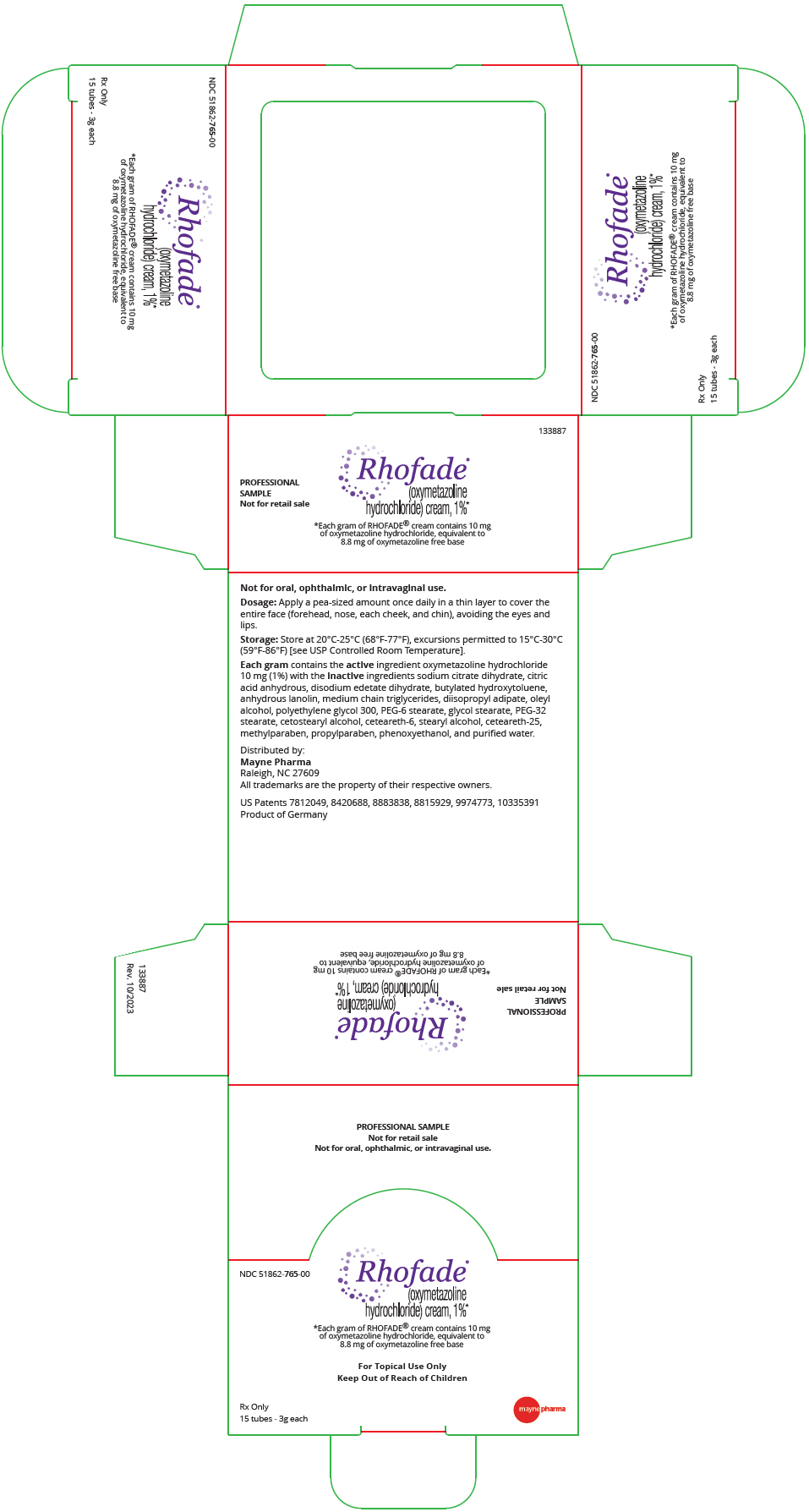 DRUG LABEL: Rhofade
NDC: 51862-765 | Form: CREAM
Manufacturer: Mayne Pharma
Category: prescription | Type: HUMAN PRESCRIPTION DRUG LABEL
Date: 20250627

ACTIVE INGREDIENTS: oxymetazoline hydrochloride 10 mg/1 g
INACTIVE INGREDIENTS: trisodium citrate dihydrate; ANHYDROUS CITRIC ACID; edetate disodium; butylated hydroxytoluene; lanolin; MEDIUM-CHAIN TRIGLYCERIDES; diisopropyl adipate; oleyl alcohol; polyethylene glycol 300; PEG-6 stearate; glycol stearate; cetostearyl alcohol; ceteareth-6; stearyl alcohol; ceteareth-25; methylparaben; propylparaben; phenoxyethanol; water; PEG-32 stearate

HIGHLIGHTS OF PRESCRIBING INFORMATION

These highlights do not include all the information needed to use RHOFADE® topical cream safely and effectively. See full prescribing information for RHOFADE® topical cream.
RHOFADE® (oxymetazoline hydrochloride) cream, 1%, for topical use
Initial U.S. Approval: 1964

1 INDICATIONS AND USAGE

Rhofade cream is an alpha1A adrenoceptor agonist indicated for the topical treatment of persistent facial erythema associated with rosacea in adults. (1)

2 DOSAGE AND ADMINISTRATION

- Not for oral, ophthalmic, or intravaginal use. (2)
- Prime pump bottle before initial use and discard product from first three pumps. (2)
- Apply a pea-sized amount once daily in a thin layer to cover the entire face (forehead, nose, each cheek, and chin) avoiding the eyes and lips. (2)
- Wash hands after application. (2)

3 DOSAGE FORMS AND STRENGTHS

Cream, 1%. Each gram of cream contains 10 mg (1%) oxymetazoline hydrochloride, equivalent to 8.8 mg (0.88%) of oxymetazoline free base. (3)

4 CONTRAINDICATIONS

- None. (4)

5 WARNINGS AND PRECAUTIONS

- Alpha-adrenergic agonists as a class may impact blood pressure. Advise patients with cardiovascular disease, orthostatic hypotension, and/or uncontrolled hypertension or hypotension to seek medical care if their condition worsens. (5.1)
- Use with caution in patients with cerebral or coronary insufficiency, Raynaud's phenomenon, thromboangiitis obliterans, scleroderma, or Sjögren's syndrome and advise patients to seek medical care if signs and symptoms of potentiation of vascular insufficiency develop. (5.2)
- Advise patients to seek immediate medical care if signs and symptoms of acute narrow-angle glaucoma develop. (5.3)

6 ADVERSE REACTIONS

Most common adverse reactions (incidence ≥ 1%) are application site dermatitis, worsening inflammatory lesions of rosacea, application site pruritis, application site erythema, and application site pain. (6.1)

To report SUSPECTED ADVERSE REACTIONS, contact Mayne Pharma at 1-844-825-8500 or FDA at 1-800-FDA-1088 or www.fda.gov/medwatch.

FULL PRESCRIBING INFORMATION

1 INDICATIONS AND USAGE

RHOFADE® (oxymetazoline hydrochloride) cream, 1% is indicated for the topical treatment of persistent facial erythema associated with rosacea in adults.

2 DOSAGE AND ADMINISTRATION

For topical use only. RHOFADE cream is not for oral, ophthalmic, or intravaginal use.

Apply a pea-sized amount of RHOFADE cream, once daily in a thin layer to cover the entire face (forehead, nose, each cheek, and chin) avoiding the eyes and lips. Wash hands immediately after applying RHOFADE cream.

3 DOSAGE FORMS AND STRENGTHS

RHOFADE® (oxymetazoline hydrochloride) cream, 1% is a white to off-white cream. Each gram of cream contains 10 mg (1%) oxymetazoline hydrochloride, equivalent to 8.8 mg (0.88%) of oxymetazoline free base.

4 CONTRAINDICATIONS

None.

5 WARNINGS AND PRECAUTIONS

5.1 Potential Impacts on Cardiovascular Disease

Alpha-adrenergic agonists may impact blood pressure. RHOFADE cream should be used with caution in patients with severe or unstable or uncontrolled cardiovascular disease, orthostatic hypotension, and uncontrolled hypertension or hypotension. Advise patients with cardiovascular disease, orthostatic hypotension, and/or uncontrolled hypertension/hypotension to seek immediate medical care if their condition worsens.

5.2 Potentiation of Vascular Insufficiency

RHOFADE cream should be used with caution in patients with cerebral or coronary insufficiency, Raynaud's phenomenon, thromboangitis obliterans, scleroderma, or Sjögren's syndrome. Advise patients to seek immediate medical care if signs and symptoms of potentiation of vascular insufficiency develop.

5.3 Risk of Angle Closure Glaucoma

RHOFADE cream may increase the risk of angle closure glaucoma in patients with narrow-angle glaucoma. Advise patients to seek immediate medical care if signs and symptoms of acute angle closure glaucoma develop.

6 ADVERSE REACTIONS

6.1 Clinical Studies Experience

Because clinical trials are conducted under varying conditions, adverse reaction rates observed in the clinical trials of a drug cannot be directly compared to rates in the clinical trials of another drug and may not reflect the rates observed in practice.

A total of 489 subjects with persistent facial erythema associated with rosacea were treated with RHOFADE cream once daily for 4 weeks in 3 controlled clinical trials. An additional 440 subjects with persistent facial erythema associated with rosacea were also treated with RHOFADE cream once daily for up to one year in a long-term (open- label) clinical trial. Adverse reactions that occurred in at least 1% of subjects treated with RHOFADE cream through 4 weeks of treatment are presented in Table 1 below.

Table 1: Adverse Reactions Reported by ≥ 1% of Subjects through 4 Weeks of Treatment in Controlled Clinical Trials
Adverse Reaction | Pooled Controlled Clinical Trials
Adverse Reaction | RHOFADE Cream (N = 489) | Vehicle Cream (N = 483)
Application site dermatitis | 9 (2%) | 0
Worsening inflammatory lesions of rosacea | 7 (1%) | 1 (<1%)
Application site pruritus | 5 (1%) | 4 (1%)
Application site erythema | 5 (1%) | 2 (<1%)
Application site pain | 4 (1%) | 1 (<1%)

In the long-term (open-label) clinical trial, the rates of adverse reactions over a one-year treatment period were as follows: worsening inflammatory lesions of rosacea (3%), application site dermatitis (3%), application site pruritis (2%), application site pain (2%), and application site erythema (2%). Subjects with persistent erythema along with inflammatory lesions were allowed to use additional therapy for the inflammatory lesions of rosacea.

7 DRUG INTERACTIONS

7.1 Anti-hypertensives/Cardiac Glycosides

Alpha-adrenergic agonists, as a class, may impact blood pressure. Caution in using drugs such as beta-blockers, anti-hypertensives and/or cardiac glycosides is advised.

Caution should also be exercised in patients receiving alpha1 adrenergic receptor antagonists such as in the treatment of cardiovascular disease, benign prostatic hypertrophy, or Raynaud's disease.

7.2 Monoamine Oxidase Inhibitors

Caution is advised in patients taking MAO inhibitors which can affect the metabolism and uptake of circulating amines.

8 USE IN SPECIFIC POPULATIONS

8.1 Pregnancy

Risk Summary

There are no available data on RHOFADE cream use in pregnant women to inform a drug-associated risk for major birth defects and miscarriage. A literature article describing intranasal decongestant use in pregnant women identified a potential association between second-trimester exposure to oxymetazoline (with no decongestant exposure in the first trimester) and renal collecting system anomalies [see Data]. In animal reproduction studies, there were no adverse developmental effects observed after oral administration of oxymetazoline hydrochloride in pregnant rats and rabbits at systemic exposures up to 3 times and 73 times, respectively, the exposure associated with the maximum recommended human dose (MRHD) [see Data]. The estimated background risks of major birth defects and miscarriage for the indicated population are unknown. All pregnancies have a background risk of birth defect, loss, or other adverse outcomes. In the U.S. general population, the estimated background risk of major birth defects and miscarriage in clinically recognized pregnancies is 2-4% and 15-20%, respectively.

Clinical Considerations

Fetal/Neonatal Adverse Reactions

Following repeated use of oxymetazoline hydrochloride solution nasal spray for the treatment of nasal congestion at a dose 5 times higher than recommended, one case of fetal distress was reported in a 41-week pregnant patient. The fetal distress resolved hours later, prior to the delivery of the healthy infant. The anticipated exposures for the case are 8- to 18-fold higher than plasma exposures after topical administration of RHOFADE cream.

Data

Human Data

No adequate and well-controlled trials of RHOFADE cream have been conducted in pregnant women. Across all clinical trials of RHOFADE cream, two pregnancies were reported. One pregnancy resulted in the delivery of a healthy child. One pregnancy resulted in a spontaneous abortion, which was considered to be unrelated to the trial medication. A literature article summarizing the results of exploratory analyses of intranasal decongestant use during pregnancy identified a potential association between second-trimester exposure to oxymetazoline hydrochloride solution (with no decongestant exposure in the first trimester) and renal collecting system anomalies.

Animal Data

Effects on embryo-fetal development were evaluated in rats and rabbits following oral administration of oxymetazoline hydrochloride during the period of organogenesis. Oxymetazoline hydrochloride did not cause adverse effects to the fetus at oral doses up to 0.2 mg/kg/day in pregnant rats during the period of organogenesis (3 times the MRHD on an AUC comparison basis). Oxymetazoline hydrochloride did not cause adverse effects to the fetus at oral doses up to 1 mg/kg/day in pregnant rabbits during the period of organogenesis (73 times the MRHD on an AUC comparison basis). Maternal toxicity, such as decreased maternal body weight, was produced at the high dose of 1 mg/kg/day in pregnant rabbits and was associated with findings of delayed skeletal ossification.

In a rat perinatal and postnatal development study, oxymetazoline hydrochloride was orally administered to pregnant rats once daily from gestation day 6 through lactation day 20. Maternal toxicity was produced at the high dose of 0.2 mg/kg/day (3 times the MRHD on an AUC comparison basis) in pregnant rats and was associated with an increase in pup mortality and reduced pup body weights. Delayed sexual maturation was noted at 0.1 and 0.2 mg/kg/day (2 times the MRHD and 3 times the MRHD on an AUC comparison basis, respectively). Oxymetazoline hydrochloride did not have any adverse effects on fetal development at a dose of 0.05 mg/kg/day (one-half of the MRHD on an AUC comparison basis).

8.2 Lactation

No clinical data are available to assess the effects of oxymetazoline on the quantity or rate of breastmilk production, or to establish the level of oxymetazoline present in human breastmilk post-dose. Oxymetazoline was detected in the milk of lactating rats. The developmental and health benefits of breastfeeding should be considered along with the mother's clinical need for RHOFADE cream and any potential adverse effects on the breastfed child from RHOFADE cream or from the underlying maternal condition.

8.4 Pediatric Use

Safety and effectiveness of RHOFADE cream have not been established in pediatric patients below the age of 18 years.

8.5 Geriatric Use

One hundred and ninety-three subjects aged 65 years and older received treatment with RHOFADE cream (n = 135) or vehicle (n = 58) in clinical trials. No overall differences in safety or effectiveness were observed between subjects ≥ 65 years of age and younger subjects, based on available data. Clinical studies of RHOFADE cream did not include sufficient numbers of subjects aged 65 and over to determine whether they respond differently from younger subjects.

10 OVERDOSAGE

RHOFADE cream is not for oral use. If oral ingestion occurs, seek medical advice. Monitor patient closely and administer appropriate supportive measures as necessary. Accidental ingestion of topical solutions (nasal sprays) containing imidazoline derivatives (e.g., oxymetazoline) in children has resulted in serious adverse events requiring hospitalization, including nausea, vomiting, lethargy, tachycardia, decreased respiration, bradycardia, hypotension, hypertension, sedation, somnolence, mydriasis, stupor, hypothermia, drooling, and coma. Keep RHOFADE cream out of reach of children.

11 DESCRIPTION

RHOFADE® (oxymetazoline hydrochloride) cream, 1% contains oxymetazoline hydrochloride, an alpha1A adrenoceptor agonist. RHOFADE is a white to off-white cream. It has a chemical name of 3-[(4,5-Dihydro1H-imidazol-2-yl)methyl]-6-(1,1-dimethylethyl)- 2,4-dimethyl-phenol hydrochloride and a molecular weight of 296.8. It is freely soluble in water and ethanol and has a partition coefficient of 0.1 in 1-octanol/water. The molecular formula of oxymetazoline HCl is C16H25ClN2O and its structural formula is:

Each gram of RHOFADE® (oxymetazoline hydrochloride) cream contains 10 mg (1%) oxymetazoline hydrochloride, equivalent to 8.8 mg (0.88%) of oxymetazoline free base. The cream contains the following inactive ingredients: sodium citrate dihydrate, citric acid anhydrous, disodium edetate dihydrate, butylated hydroxytoluene, anhydrous lanolin, medium chain triglycerides, diisopropyl adipate, oleyl alcohol, polyethylene glycol 300, PEG-6 stearate, glycol stearate, PEG-32 stearate, cetostearyl alcohol, ceteareth-6, stearyl alcohol, ceteareth-25, methylparaben, propylparaben, phenoxyethanol, and purified water.

12 CLINICAL PHARMACOLOGY

12.1 Mechanism of Action

Oxymetazoline is an alpha1A adrenoceptor agonist. Oxymetazoline acts as a vasoconstrictor.

12.2 Pharmacodynamics

The pharmacodynamics of RHOFADE cream has not been studied.

12.3 Pharmacokinetics

Absorption

The pharmacokinetics of oxymetazoline was evaluated following topical administration of RHOFADE cream in a thin layer to cover the entire face in adult subjects with erythema associated with rosacea. The median weight of cream for each dose administration was 0.3 g. Plasma oxymetazoline concentrations were measurable in most of the subjects. Following the first dose application, the mean ± standard deviation (SD) peak concentrations (Cmax) and area under the concentration-time curves from time 0 to 24 hours (AUC0-24hr) were 60.5 ± 53.9 pg/mL and 895 ±798 pg*hr/mL, respectively. Following once daily applications for 28 days, the mean ± SD Cmax and AUC0-24hr were 66.4 ± 67.1 pg/mL and 1050 ± 992 pg*hr/mL, respectively. Following twice daily applications (twice the recommended frequency of application) for 28 days, the mean ± SD Cmax and AUC0-24hr were 68.8 ± 61.1 pg/mL and 1530 ± 922 pg*hr/mL, respectively.

Distribution

An in vitro study demonstrated that oxymetazoline is 56.7% to 57.5% bound to human plasma proteins.

Metabolism

In vitro studies using human liver microsomes showed that oxymetazoline was minimally metabolized, generating mono-oxygenated and dehydrogenated products of oxymetazoline. The percentage of parent drug oxymetazoline remaining was 95.9% after a 120-minute incubation with human liver microsomes.

Excretion

The excretion of oxymetazoline following administration of RHOFADE cream has not been characterized in humans.

Drug Interaction

In vitro studies using human liver microsomes demonstrated that oxymetazoline up to the tested concentration of 100 nM had no inhibition on the activities of the cytochrome P450 (CYP) isoenzymes 1A2, 2B6, 2C8, 2C9, 2C19, 2D6, and 3A4/5. Treatment of cultured human hepatocytes with up to 100 nM oxymetazoline did not induce CYP1A2, CYP2B6, or CYP3A4.

13 NONCLINICAL TOXICOLOGY

13.1 Carcinogenesis, Mutagenesis, Impairment of Fertility

Oxymetazoline hydrochloride was not associated with an increased incidence of neoplastic or proliferative changes in transgenic mice given oral doses of 0.5, 1.0, or 2.5 mg/kg/day oxymetazoline hydrochloride for 6 months.

Oxymetazoline hydrochloride revealed no evidence of mutagenic or clastogenic potential based on the results of two in vitro genotoxicity tests (Ames assay and human lymphocyte chromosomal aberration assay) and one in vivo genotoxicity test (mouse micronucleus assay).

Effects on fertility and early embryonic development were evaluated in rats following oral administration of 0.05, 0.1, or 0.2 mg/kg/day oxymetazoline hydrochloride prior to and during mating and through early pregnancy. Decreased number of corpora lutea and increased post-implantation losses were noted at 0.2 mg/kg/day oxymetazoline hydrochloride (3 times the MRHD on an AUC comparison basis). However, no treatment related effects on fertility or mating parameters were noted at 0.2 mg/kg/day oxymetazoline hydrochloride (3 times the MRHD on an AUC comparison basis).

14 CLINICAL STUDIES

RHOFADE cream was evaluated for the treatment of persistent erythema associated with rosacea in two identical, randomized, double-blind, vehicle-controlled, parallel-group clinical trials. The trials enrolled 885 subjects aged 18 years and older. Overall, 90% of subjects were Caucasian and 79% were female. Subjects applied either RHOFADE cream or vehicle once daily for 29 days.

Disease severity was graded by the clinician using a 5-point clinician erythema assessment (CEA) scale and by the subject on a similar 5-point subject self-assessment (SSA) scale, on which subjects scored either "moderate" or "severe" on both scales.

CEA and SSA were measured over a 12-hour period at equally-spaced timepoints (hours 3, 6, 9, and 12) post dose on Days 1, 15, and 29. The primary efficacy endpoint was defined as the proportion of subjects with at least a 2-grade reduction in erythema (improvement) from baseline (pre-dose on Day 1) on both the CEA and SSA measured at hours 3, 6, 9, and 12 on Day 29. The results from both trials on the composite endpoint for Day 29 are presented in Table 2.

Table 2: Proportion of Subjects Achieving Composite Success [Composite success is defined as the proportion of subjects achieving at least a 2-grade improvement on both CEA and SSA.] on Day 29
Time-point (Hour) | Trial 1 |  | Trial 2
Time-point (Hour) | RHOFADE Cream (N-222) | Vehicle Cream (N-218) | RHOFADE Cream (N-224) | Vehicle Cream (N-221)
3 | 12% | 6% | 14% | 7%
6 | 16% | 8% | 13% | 5%
9 | 18% | 6% | 16% | 9%
12 | 15% | 6% | 12% | 6%

16 HOW SUPPLIED/STORAGE AND HANDLING

RHOFADE® (oxymetazoline hydrochloride) cream, 1%, is a white to off-white cream. The product is available in a laminated tube in the following packaging configuration, each with a child-resistant closure:

NDC 51862-765-30 | 30 gram tube

STORAGE AND HANDLING

Storage: Store at 20°C-25°C (68°F-77°F); excursions permitted to 15°C-30ºC (59°F- 86ºF) [see USP Controlled Room Temperature].

17 PATIENT COUNSELING INFORMATION

Advise the patient and/or caregiver to read the FDA-approved patient labeling (Patient Information and Instructions for Use).

Important Administration Instructions

Advise patients of the following:

- RHOFADE cream is for topical use only.
- Do not apply RHOFADE cream to irritated skin or open wounds.\
- Avoid contact with the eyes and lips.
- Wash hands immediately after application.
- Keep RHOFADE cream out of reach of children.

Distributed by:
Mayne Pharma
Raleigh, NC 27609

RHOFADE and its design are registered trademarks of Mayne Pharma, LLC

Patented. U.S. Patent Numbers: U.S. 7,812,049; U.S. 8,420,688; U.S. 8,815,929; U.S. 8,883,838; U.S. 9,974,773 and U.S. 10335391. Product of Germany.

PATIENT INFORMATION
RHOFADE® (roe' fayd)
(oxymetazoline hydrochloride) cream

Important: RHOFADE cream is for skin (topical) use on the face only. Do not use RHOFADE cream in your eyes, mouth, or vagina.

Keep RHOFADE cream out of the reach of children.

Get medical help right away if you, a child, or anyone else swallows RHOFADE cream.

What is RHOFADE cream?

RHOFADE cream is a prescription medicine used on the skin (topical) to treat facial redness due to rosacea that does not go away (persistent) in adults.

It is not known if RHOFADE cream is safe and effective in children under 18 years of age.

Before you use RHOFADE cream, tell your healthcare provider about all of your medical conditions, including if you:

- have heart, blood vessel, or blood pressure problems. Call your healthcare provider or get medical help if these conditions worsen.
- have problems with blood circulation or have had a stroke
- have Sjögren's Syndrome
- have scleroderma
- have Raynaud's phenomenon
- have thromboangitis obliterans
- have narrow-angle glaucoma. Call your healthcare provider or get medical help if your glaucoma worsens.
- have irritated skin or open sores on the face
- are pregnant or plan to become pregnant. It is not known if RHOFADE cream will harm your unborn baby.
- are breastfeeding. It is not known if RHOFADE cream passes into your breast milk. Talk to your healthcare provider about the best way to feed your baby if you use RHOFADE cream.

Tell your healthcare provider about all the medicines you take, including prescription and over-the-counter medicines, skin products, vitamins, and herbal supplements. Using RHOFADE cream with certain other medicines may affect each other and can cause serious side effects.

How should I use RHOFADE cream?

- See the detailed Instructions for Use that comes with your RHOFADE cream tube or pump for information about how to apply RHOFADE cream correctly.
- Use RHOFADE cream exactly as your healthcare provider tells you. Do not use more RHOFADE cream than prescribed.
- RHOFADE cream is for use on your skin only. Do not use RHOFADE cream in your eyes, mouth, or vagina. Avoid contact with your lips and eyes.
- Do not apply RHOFADE cream to irritated skin or open wounds.

What are the possible side effects of RHOFADE cream?

The most common side effects of RHOFADE cream include application site reactions of:

- skin reactions (dermatitis)
- worsening of rosacea pimples
- itching
- redness
- pain

These are not all the possible side effects of RHOFADE cream.

Call your doctor for medical advice about side effects. You may report side effects to FDA at 1-800-FDA-1088.

How should I store RHOFADE cream?

- Store RHOFADE cream at room temperature between 68°F to 77°F (20°C to 25°C).

Keep RHOFADE cream and all medicines out of the reach of children.

General information about the safe and effective use of RHOFADE cream

Medicines are sometimes prescribed for purposes other than those listed in a Patient Information leaflet. Do not use RHOFADE cream for a condition for which it was not prescribed. Do not give RHOFADE cream to other people, even if they have the same symptoms that you have. It may harm them. You can ask your pharmacist or healthcare provider for information about RHOFADE cream that is written for health professionals.

What are the ingredients in RHOFADE cream?

Active ingredient: oxymetazoline hydrochloride

Inactive ingredients: sodium citrate dihydrate, citric acid anhydrous, disodium edetate dihydrate, butylated hydroxytoluene, anhydrous lanolin, medium chain triglycerides, diisopropyl adipate, oleyl alcohol, polyethylene glycol 300, PEG-6 stearate, glycol stearate, PEG-32 stearate, cetostearyl alcohol, ceteareth-6, stearyl alcohol, ceteareth-25, methylparaben, propylparaben, phenoxyethanol, and purified water

Distributed by:
Mayne Pharma
Raleigh, NC 27609

RHOFADE and its design are registered trademarks of Mayne Pharma, LLC.

Patented. U.S. Patent Numbers: U.S. 7,812,049; U.S. 8,420,688; U.S. 8,815,929; U.S. 8,883,838; U.S. 9,974,773 and U.S. 10335391. Product of Germany.

This Patient Information has been approved by the U.S. Food and Drug Administration

Revised 10/2023

INSTRUCTIONS FOR USE
RHOFADE® (roe' fayd)
(oxymetazoline hydrochloride) cream
Tube

Important:

- RHOFADE cream is for skin (topical) use on the face only. Do not use RHOFADE cream in your eyes, mouth, or vagina.
- Keep RHOFADE cream out of the reach of children.
- Get medical help right away if you, a child, or anyone else swallows RHOFADE cream.

Read and follow the steps below so that you use your tube of RHOFADE cream correctly:

Step 1: Open the tube of RHOFADE cream by gently pressing down on the child-resistant cap and twisting it counterclockwise until the cap is removed. Do not squeeze the tube while opening or closing.
Note: When the cap is removed, the tube is not child-resistant.

Step 2: To apply RHOFADE cream to your face, squeeze a pea- sized amount of RHOFADE cream from the tube onto your fingertip.

Step 3: Apply the pea-sized amount of RHOFADE cream to cover your entire face (forehead, nose, each cheek, and chin) 1 time each day. Spread the cream smoothly and evenly in a thin layer over your face.

- Avoid contact with your eyes and lips.
- Do not apply cream to irritated skin or open wounds.

Step 4: To close your RHOFADE cream tube, place the cap back on the tube. Press down on the child-resistant cap and twist clockwise until it stops. The tube is child-resistant again.

Step 5: Wash your hands right away after applying RHOFADE cream.

How do I store RHOFADE cream?

- Store RHOFADE cream at room temperature between 68°F to 77°F (20°C to 25°C).
- Keep RHOFADE cream and al medicines out of the reach of children.

This Instructions for Use has been approved by the U.S. Food and Drug Administration.

Distributed by:
Mayne Pharma
Raleigh, NC 27609

RHOFADE and its design are registered trademarks of Mayne Pharma, LLC

Patented. U.S. Patent Numbers: U.S. 7,812,049; U.S. 8,420,688; U.S. 8,815,929; U.S. 8,883,838; U.S. 9,974,773 and U.S. 10335391. Product of Germany.

Revised: 10/2023

PRINCIPAL DISPLAY PANEL - 30 g Tube Carton

NDC 51862-765-30

Rhofade®
(oxymetazoline
hydrochloride) cream, 1%*

*Each gram of RHOFADE® cream
contains 10 mg of oxymetazoline
hydrochloride, equivalent to
8.8 mg of oxymetazoline free base

For Topical Use Only
Keep Out of Reach of Children

Rx Only
30 g

mayne pharma

PRINCIPAL DISPLAY PANEL - 3g Tube Carton

NDC 51862-765-00

Rhofade®
(oxymetazoline
hydrochloride) cream, 1%*

*Each gram of RHOFADE® cream contains 10 mg
of oxymetazoline hydrochloride, equivalent to
8.8 mg of oxymetazoline free base

For Topical Use Only
Keep Out of Reach of Children

Rx Only
15 tubes - 3g each

mayne pharma